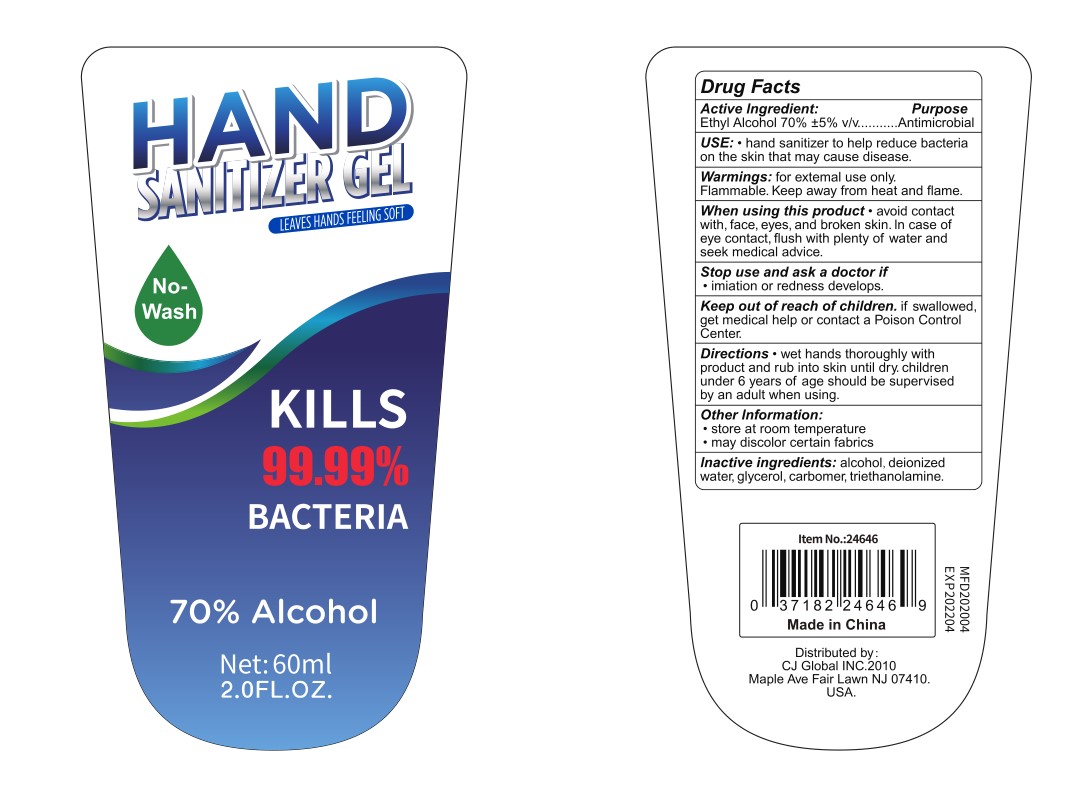 DRUG LABEL: 70% alcohol Hand Sanitizer Gel
NDC: 77372-001 | Form: GEL
Manufacturer: CJ Global Inc
Category: otc | Type: HUMAN OTC DRUG LABEL
Date: 20200506

ACTIVE INGREDIENTS: ALCOHOL 68 mL/100 mL
INACTIVE INGREDIENTS: GLYCERIN 1 mL/100 mL; WATER; CARBOMER 940 0.4 mL/100 mL; TROLAMINE 0.4 mL/100 mL

NDC registration

Active Ingredient(s)

Ethyl Alcohol 70%±5 v/v. Purpose: Antimicrobial

Purpose

purpose:Antimicrobial

Use

Hand Sanitizer to help reduce bacteria on the skin that may cause disease.

Warnings

For external use only. Flammable. Keep away from heat or flame

When using this product avoid contact with face, eyes, and broken skin . In case of eye contact , flush with plenty of water and seek medical advice.

Stop use and ask a doctor if imiation or redness develops.

Keep out of reach of children. If swallowed, get medical help or contact a Poison Control Center right away.

Directions

wet hands thoroughly with product and rub into skin until dry. children under 6years of age should be supervised by an adult when using.

Other information

Store at room temperature,may discolor certain fabrics

Package Label - Principal Display Panel

60ml NDC:77372-001-01